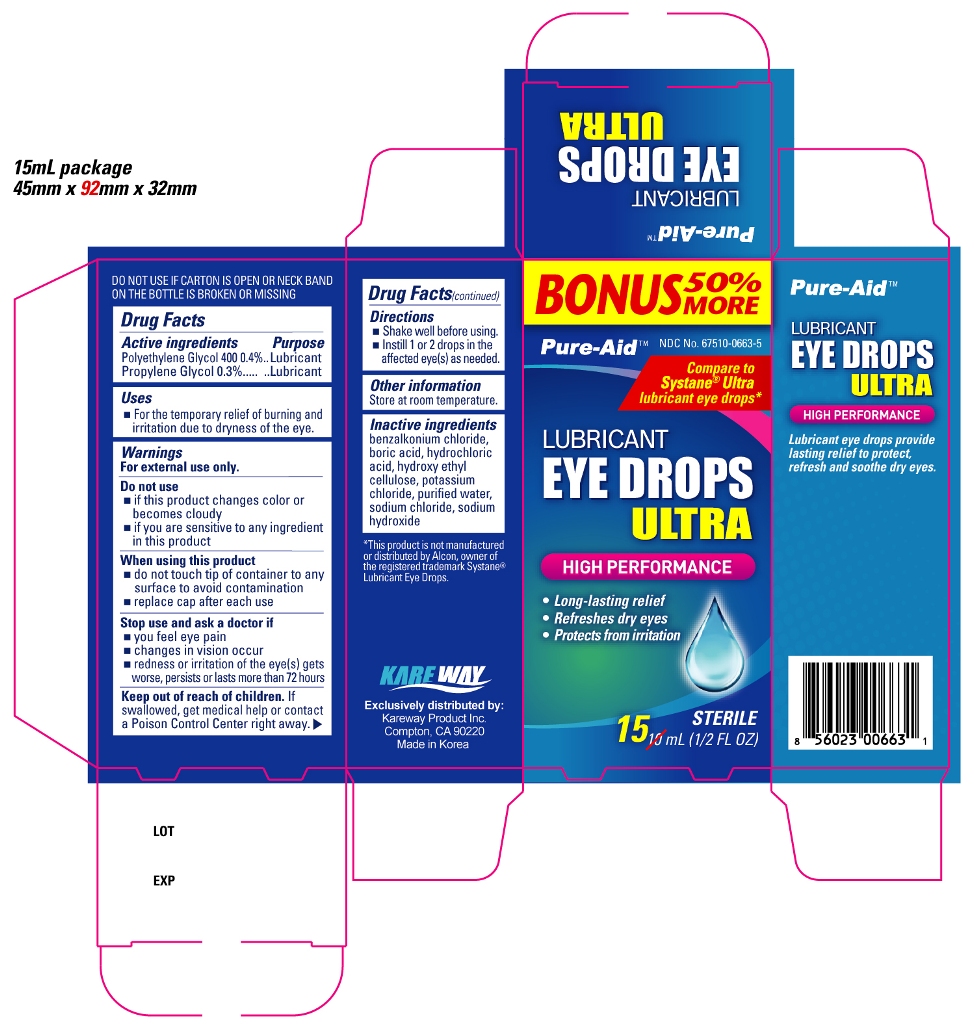 DRUG LABEL: Eye Lubricant 
NDC: 67510-0663 | Form: LIQUID
Manufacturer: Kareway Product, Inc.
Category: otc | Type: HUMAN OTC DRUG LABEL
Date: 20120621

ACTIVE INGREDIENTS: POLYETHYLENE GLYCOL 400 4 mg/1 mL; PROPYLENE GLYCOL 3 mg/1 mL
INACTIVE INGREDIENTS: BENZALKONIUM CHLORIDE; BORIC ACID; HYDROCHLORIC ACID; POTASSIUM CHLORIDE; WATER; SODIUM CHLORIDE; SODIUM HYDROXIDE

Drug Facts

Active ingredients

Polyethylene Glycol 400 0.4%

Propylene Glycol 0.3%

Purpose

Lubricant

Lubricant

Uses

- for the temporary relief of burning and irritation due to dryness of the eye
- for protection against further irritation

Warnings

Enter section text here

When using this product

- remove contact lenses before using
- do not use if this solution changes color or becomes cloudy
- do not touch tip of container to any surface to avoid contamination
- replace cap after each use

Stop use and ask a doctor if

- you feel eye pain
- changes in vision occur
- redness or irritation of the eyes lasts
- condition worsens or lasts more than 72 hours

If pregnant or breast-feeding,

ask a health professional before use.

Keep out of reach of children.

If swallowed, get medical help or contact a Poison Control Center right away.

Directions

- Put 1 to 2 drops in the affected eye(s) as needed
- children under 6 years of age: ask a doctor

Other information

Store at 15 - 30ºC (59 - 86ºF)

Inactive ingredients

benzalkonium chloride, boric acid, hydrochloric acid, hydroxyethyl cellulose, potassium chloride, purified water, sodium chloride, sodium hydroxide

PACKAGE LABEL

Lubricant Eye Drops Ultra